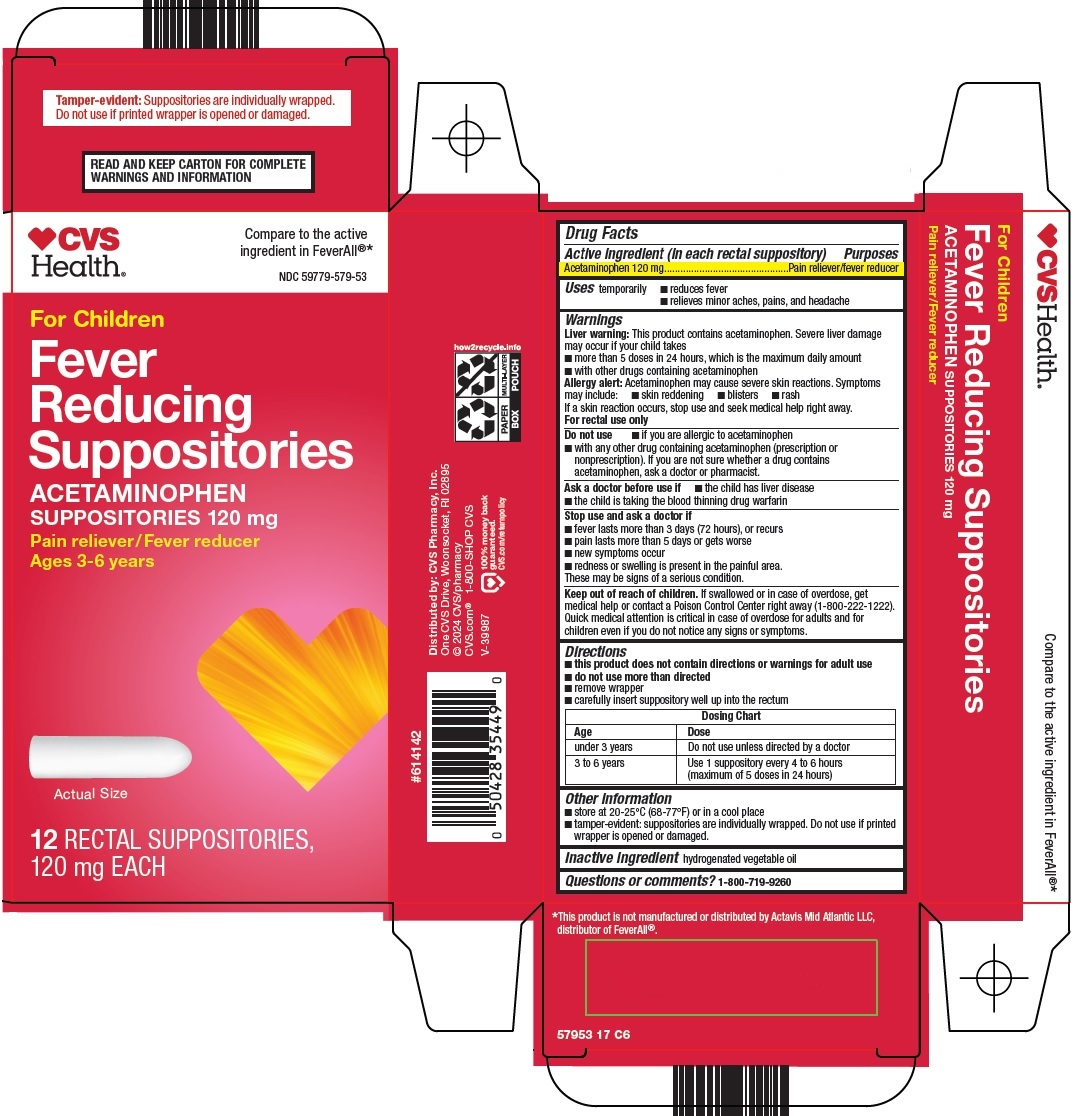 DRUG LABEL: fever reducing
NDC: 59779-579 | Form: SUPPOSITORY
Manufacturer: CVS Pharmacy
Category: otc | Type: HUMAN OTC DRUG LABEL
Date: 20250606

ACTIVE INGREDIENTS: ACETAMINOPHEN 120 mg/1 1
INACTIVE INGREDIENTS: COTTONSEED OIL

CVS Pharmacy, Inc. Fever Reducing Suppositories Drug Facts

Active ingredient (in each rectal suppository)

Acetaminophen 120 mg

Purposes

Pain reliever/fever reducer

Uses

temporarily

- reduces fever
- relieves minor aches, pains, and headache

Warnings

Liver warning: This product contains acetaminophen. Severe liver damage may occur if your child takes

- more than 5 doses in 24 hours, which is the maximum daily amount
- with other drugs containing acetaminophen

Allergy alert: Acetaminophen may cause severe skin reactions. Symptoms may include:

- skin reddening
- blisters
- rash

If a skin reaction occurs, stop use and seek medical help right away.

For rectal use only

Do not use

- if you are allergic to acetaminophen
- with any other drug containing acetaminophen (prescription or nonprescription). If you are not sure whether a drug contains acetaminophen, ask a doctor or pharmacist.

Ask a doctor before use if

- your child has liver disease
- your child is taking the blood thinning drug warfarin

Stop use and ask a doctor if

- fever lasts more than 3 days (72 hours), or recurs
- pain lasts more than 5 days or gets worse.
- new symptoms occur.
- redness or swelling is present in the painful area.

These may be signs of a serious condition.

Keep out of reach of children.

If swallowed or in case of overdose, get medical help or contact a Poison Control Center right away (1-800-222-1222). Quick medical attention is critical in case of overdose for adults and for children even if you do not notice any signs or symptoms.

Directions

- this product does not contain directions or warnings for adult use
- do not use more than directed
- remove wrapper
- carefully insert suppository well up into the rectum

Dosing Chart
Age | Dose
under 3 years | Do not use unless directed by a doctor
3 to 6 years | Use 1 suppository every 4 to 6 hours (maximum of 5 doses in 24 hours)

Other information

- store at 20-25°C (68-77°F) or in a cool place
- tamper-evident: suppositories are individually wrapped. Do not use if printed wrapper is opened or damaged.

Inactive ingredients

hydrogenated vegetable oil

Questions or comments?

1-800-719-9260

Principal Display Panel

CVS Health®

Compare to the active ingredient in FeverAll®

For Children

Fever Reducing Suppositories

ACETAMINOPHEN SUPPOSITORIES 120 mg

Pain reliever/Fever reducer

Ages 3-6 years

Actual Size

12 RECTAL SUPPOSITORIES, 120 mg EACH